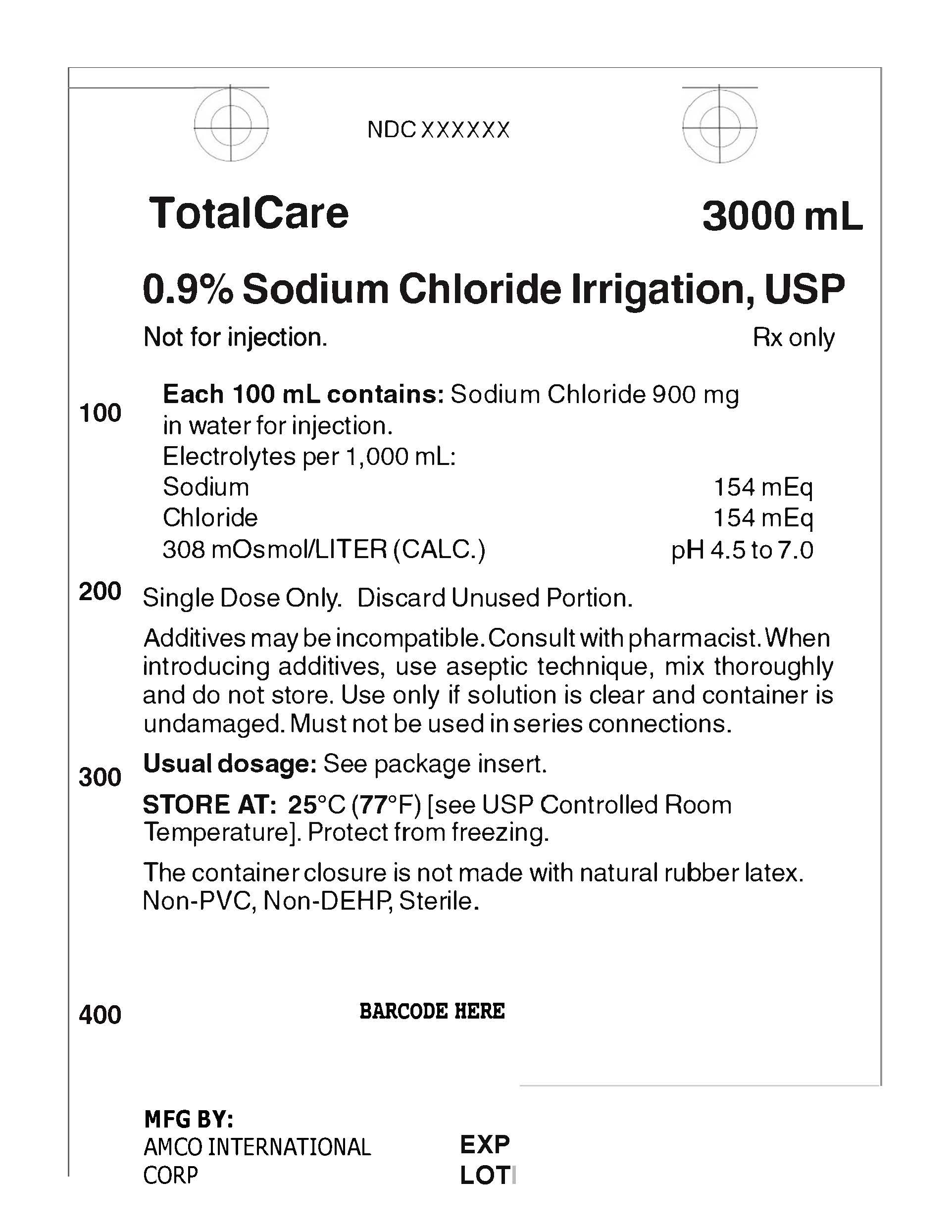 DRUG LABEL: 0.9% SODIUM CHLORIDE IRRIGATION
NDC: 84866-6670 | Form: IRRIGANT
Manufacturer: AMCO INTERNATIONAL CORP
Category: prescription | Type: HUMAN PRESCRIPTION DRUG LABEL
Date: 20241216

ACTIVE INGREDIENTS: SODIUM CHLORIDE 900 mg/100 mL
INACTIVE INGREDIENTS: WATER

Directions for Use of Flexible Plastic Irrigation Containers

If desired, warm in overwrap to near body temperature in a water bath or oven heated to not more than 45°C. Parenteral drug products should be inspected visually for particulate matter and discoloration prior to administration whenever solution and container permit.

DIRECTIONS FOR USE

Tear overwrap down side at slit and remove solution container. Visually inspect the container. If the outlet port protector is damaged, detached, or not present, discard container as solution path sterility may be impaired. Some opacity of the plastic due to moisture absorption during the sterilization process may be observed. This is normal and does not affect the solution quality or safety. The opacity will diminish gradually. Check for minute leaks by squeezing bag firmly. If leaks are found, discard solution as sterility may be impaired. Use Aseptic Technique. 1.Suspend container using hanger hole. 2.Remove plastic protector from outlet port at bottom of container 3.Attach irrigation set. Refer to complete directions accompanying set. Exposure of pharmaceutical products to heat should be minimized. Avoid excessive heat. It is recommended the product be stored at room temperature (25°C): brief exposure up to 40°C does not adversely affect the product

HEALTH CARE PROVIDER LETTER

Dear Healthcare Professional,
To prevent a drug shortage of large volume parenteral fluid drug products, we plan
to coordinate with the U.S. Food and Drug Administration (FDA) to temporarily import 0.9% Sodium Chloride IRRIGATION (3,000 mL) from specific DRE
manufacturing facilities. FDA has not approved these products manufactured by this facility. We are also working to label and produce this drug domestically in the United States.
You may be provided with additional letters for other imported products you receive. Please read each letter in its entirety because each letter may contain different product specific information.
All labels are in English with NDC listed on label.
It is important to note the following:

After opening the carton or box, the bags should be inspected visually to confirm there is no visible particulate matter or bag defects, such as leaks. Container integrity is imperative to ensure sterility of products. Parenteral drug products should be inspected visually for particulate matter and bag defects prior to administration, whenever solution or container permits.

USE A NEW BAG IF PARTICULATES ARE VISIBLE OR IF THE IV BAG CONTAINS A LEAK.
Reporting Adverse Events or Product Quality Issues
To report adverse events associated with these imported products, please call AMCO at+1 833 3 MY AMCO.
. Adverse events or quality problems experienced with the use of these imported products may also be reported to the FDA's MedWatch Adverse Event Reporting program either online, by regular mail or by fax

• Complete and submit the report Online: www.fda.gov/medwatch/report.htm
• Regular mail or Fax: Download form www.fda.gov/MedWatch/getforms.htm or call

1-800-332-1088 to request a reporting form, then complete and return to the address on the pre-addressed form, or submit by fax to 1-800-FDA-0178 (1-800-332-0178).
To report product quality issues associated with these imported products, please contact AMCO at +1 833 3 MY AMCO.
If you have any questions about the information contained in this letter or the use of the imported products, please Contact +1 833 3 MY AMCO.
To place an order, please contact AMCO at +1 833 3 MY AMCO.

PACKAGE LABEL

3000 mL NDC NOT FOR INJECTION 0.9% SODIUM CHLORIDE Irrigation USP Each 100 mL contains 900 mg Sodium Chloride USP No antimicrobial agent has been added pH 5.5 (4.5 to 7.0) mEq/L Sodium 154 Chloride 154 Osmolarity 308 mOsmol/L (calc) Sterile Nonpyrogenic Single dose container Do not use unless solution is clear Discard unused portion Cautions Squeeze and inspect inner bag which maintains product sterility Discard if leaks are found Rx Only Store unit in moisture barrier overwrap at room temperature (25°C) until ready to use Avoid excessive heat See insert 0.9% Sodium Chloride NaCl Irrigation USP